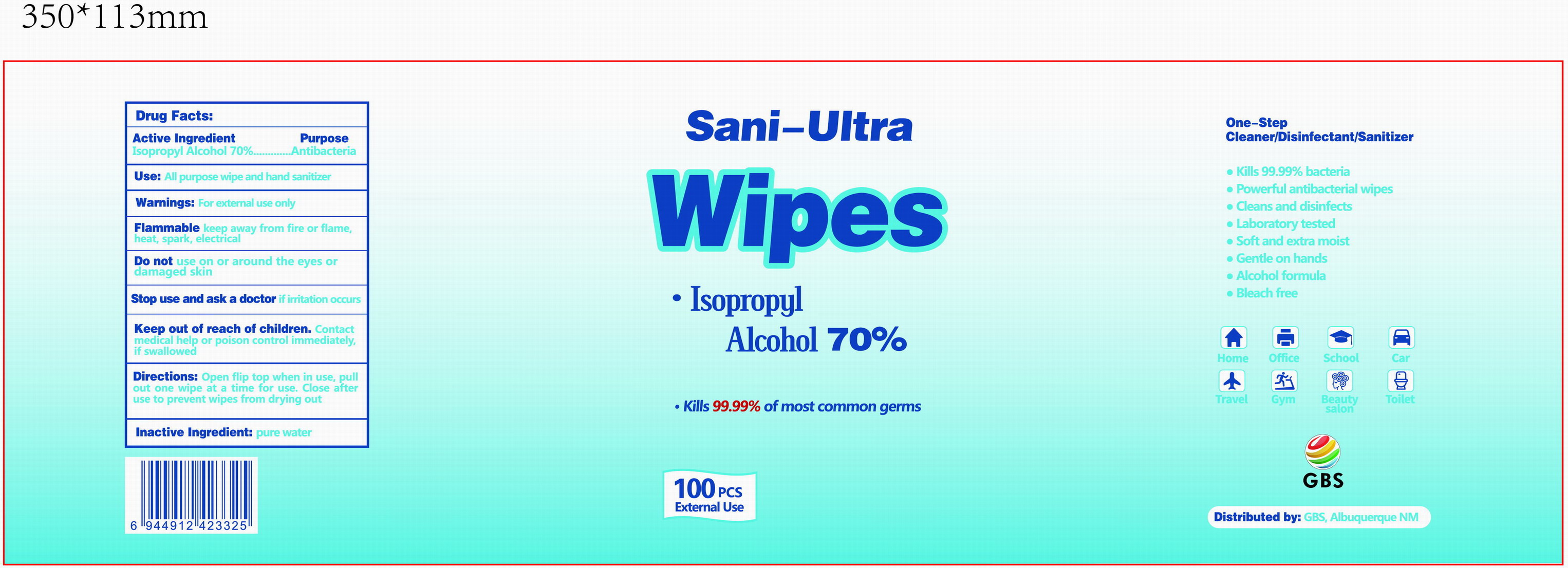 DRUG LABEL: Sani-Ultra Wipes
NDC: 78183-020 | Form: CLOTH
Manufacturer: Kunming Ansheng Industry & Trade Co., Ltd.
Category: otc | Type: HUMAN OTC DRUG LABEL
Date: 20200814

ACTIVE INGREDIENTS: ISOPROPYL ALCOHOL 0.7 U/1 U
INACTIVE INGREDIENTS: WATER

70% Isopropyl Alcohol (Sani-Ultra)

Active Ingredient(s)

Isopropyl Alcohol 70% v/v.

Purpose

Antibacterial;

Use

Hand Sanitizer to reduce bacteria.

Warnings

For external use only.

Flammable. Keep away from fire or flame, heat, spark, electrical.

Do not use on or around the eyes or damaged skin.

When using this product do not use in or contact the eyes, ears, and mouth.

Stop use and ask a doctor if irritation occurs.

Keep out of reach of children. Contact medical help or poison control immediatedly, if swallowed.

Directions

- Open flip top when in use, pull out one wipe at a time for use.
- Close after use to prevent wipes from drying out.

Inactive ingredients

Pure water

Package Label - Principal Display Panel

100 wipes in 1 canister.

NDC: 78183-020-01;